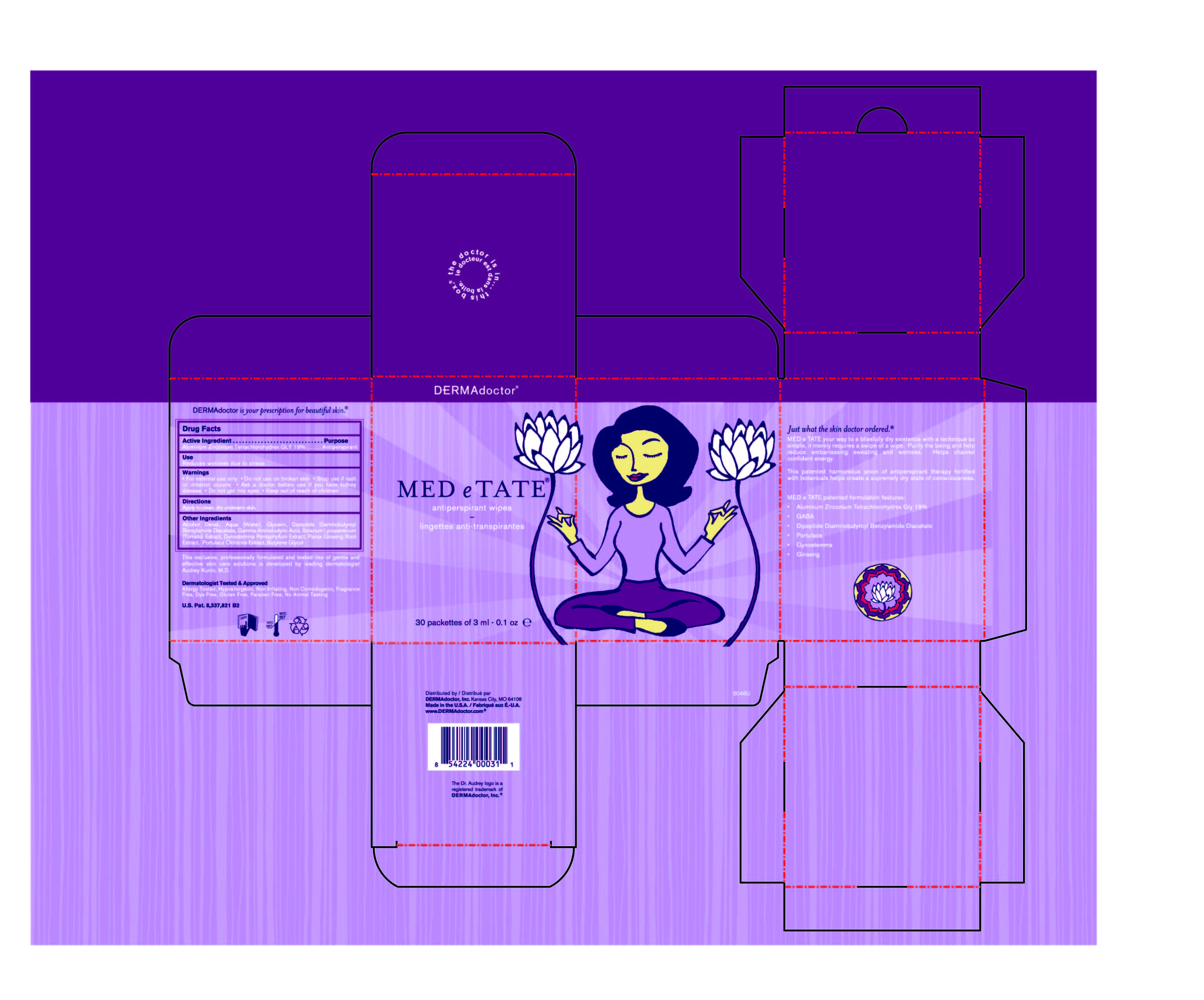 DRUG LABEL: MEDeTATE
NDC: 68715-311 | Form: LIQUID
Manufacturer: DERMAdoctor, LLC
Category: otc | Type: HUMAN OTC DRUG LABEL
Date: 20250412

ACTIVE INGREDIENTS: ALUMINUM ZIRCONIUM TETRACHLOROHYDREX GLY 19 mg/100 mL
INACTIVE INGREDIENTS: PURSLANE; BUTYLENE GLYCOL; ALCOHOL; Water; Glycerin; Dipeptide Diaminobutyroyl Benzylamide Diacetate; .GAMMA.-AMINOBUTYRIC ACID; TOMATO; GYNOSTEMMA PENTAPHYLLUM LEAF; ASIAN GINSENG

MEDeTATE

Active Ingredient

Aluminum Zirconium Tetrachlorohydrex GLY 19%

Purpose

Antiperspirant

Use

Reduces wetness due to stress

Warnings

• For external use only

• Do not use on broken skin

• Stop use if rash or irritation occurs

• Ask a doctor before use if you have kidney disease

• Do not get into eyes

• Keep out of reach of children.

Directions

Apply to clean, dry underarm skin.

Other Ingredients

Alcohol Denat., Aqua (Water), Glycerin, Dipeptide Diaminobutyroyl Benzylamide Diacetate, Gamma Aminobutyric Acid, Solanum Lycopersicum (Tomato) Extract, Gynostemma Pentaphyllum Extract, Panax Ginseng Root Extract, Portulaca Oleracea Extract, Butylene Glycol

Keep out of reach of children

purpose section

antiperspirant

administration

apply to clean dry underarm skin

Principal Display Panel MEDeTATE 30 packettes of 3 ml - 0.1 oz wipes

MEDeTATE

antiperspirant wipes

30 packettes of 3 ml - 0.1 oz wipes